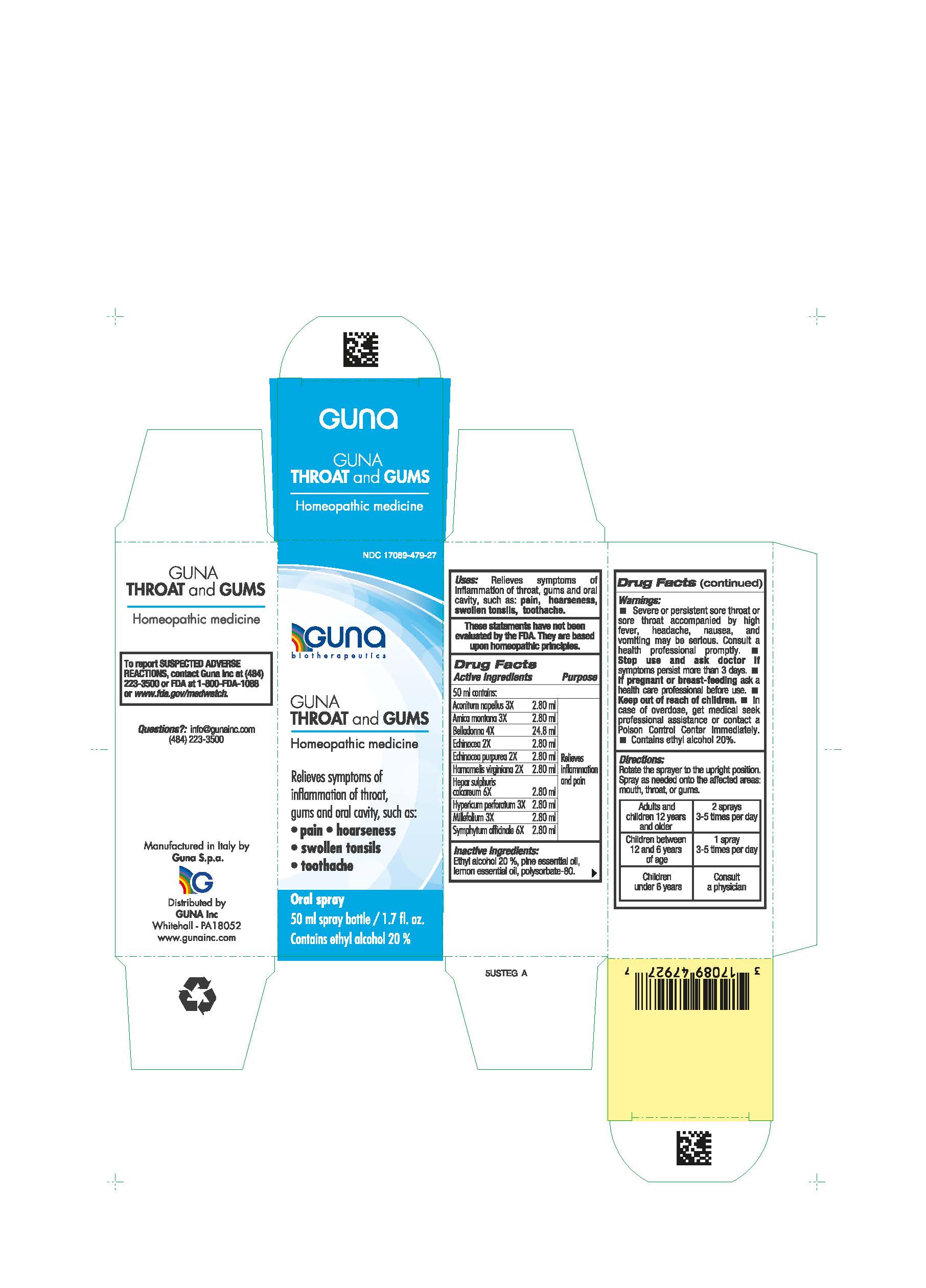 DRUG LABEL: GUNA THROAT AND GUMS
NDC: 17089-479 | Form: SPRAY
Manufacturer: Guna spa
Category: homeopathic | Type: HUMAN OTC DRUG LABEL
Date: 20210217

ACTIVE INGREDIENTS: ACONITUM NAPELLUS 3 [hp_X]/50 mL; ARNICA MONTANA 3 [hp_X]/50 mL; ATROPA BELLADONNA 4 [hp_X]/50 mL; ECHINACEA ANGUSTIFOLIA 2 [hp_X]/50 mL; ECHINACEA PURPUREA 2 [hp_X]/50 mL; WITCH HAZEL 2 [hp_X]/50 mL; CALCIUM SULFIDE 6 [hp_X]/50 mL; HYPERICUM PERFORATUM 3 [hp_X]/50 mL; ACHILLEA MILLEFOLIUM 3 [hp_X]/50 mL; COMFREY ROOT 6 [hp_X]/50 mL
INACTIVE INGREDIENTS: ABIES SACHALINENSIS VAR. SACHALINENSIS OIL; ALCOHOL; LEMON OIL; POLYSORBATE 80

GUNA THROAT AND GUMS

INACTIVE INGREDIENT

Inactive ingredients: Ethyl alcohol 20 %, pine essential oil, lemon essential oil, polysorbate-80.

INDICATIONS AND USAGE

Directions: Rotate the sprayer to the upright position. Spray as needed onto affected areas: mouth, throat, or gums.

QUESTIONS

Questions?: info@gunainc.com
(484) 223-3500

DIRECTIONS

Adults and children 12 years and older 2 sprays, 3-5 times per day
Children between 12 and 6 years of age 1 spray, 3-5 times per day
Children under 6 years consult a physician

WARNINGS

Keep out of reach of children

PREGNANCY

If pregnant or breast-feeding ask a health care professional before use

WARNINGS

- Severe or persistent sore throat or sore throat accompanied by high fever, headache, nausea, and vomiting may be serious. Consult a health professional promptly. ●Stop use and ask doctor if symptoms persist more than 3 days. ● If pregnant or breast-feeding ask a health care professional before use.● Keep out of reach of children. In case of overdose, get medical seek professional assistance or contact a Poison Control Center immediately. ● Contains ethyl alcohol 20%

USES

Relieves symptoms of inflammation of throat, gums and oral cavity, such as:

- pain
- hoarseness
- swollen tonsils
- toothache

ACTIVE INGREDIENTS/PURPOSE

Aconitum napellus 3X

Arnica montana 3X

Belladonna 4X

Echinacea 2X

Echinacea purpurea 2X

Hamamelis virginiana 2X

Hepar sulphuris calcareum 6X

Hypericum perforatum 3X

Millefolium 3X

Symphytum officinale 6X

RELIEF OF INFLAMMATION AND PAIN